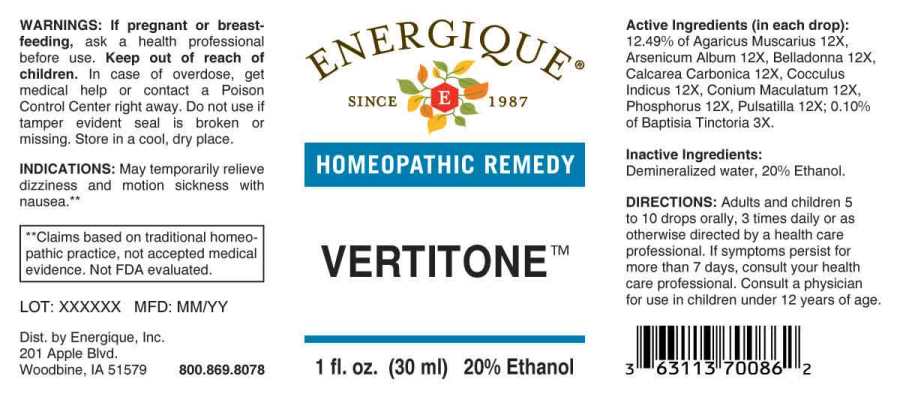 DRUG LABEL: Vertitone
NDC: 44911-0181 | Form: LIQUID
Manufacturer: Energique, Inc.
Category: homeopathic | Type: HUMAN OTC DRUG LABEL
Date: 20241031

ACTIVE INGREDIENTS: BAPTISIA TINCTORIA ROOT 3 [hp_X]/1 mL; AMANITA MUSCARIA FRUITING BODY 12 [hp_X]/1 mL; ARSENIC TRIOXIDE 12 [hp_X]/1 mL; ATROPA BELLADONNA 12 [hp_X]/1 mL; OYSTER SHELL CALCIUM CARBONATE, CRUDE 12 [hp_X]/1 mL; ANAMIRTA COCCULUS SEED 12 [hp_X]/1 mL; CONIUM MACULATUM FLOWERING TOP 12 [hp_X]/1 mL; PHOSPHORUS 12 [hp_X]/1 mL; PULSATILLA PRATENSIS WHOLE 12 [hp_X]/1 mL
INACTIVE INGREDIENTS: WATER; ALCOHOL

DRUG FACTS:

ACTIVE INGREDIENTS:

(in each drop): 12.49% of Agaricus Muscarius 12X, Arsenicum Album 12X, Belladonna 12X, Calcarea Carbonica 12X, Cocculus Indicus 12X, Conium Maculatum 12X, Phosphorus 12X, Pulsatilla (Pratensis) 12X; 0.10% of Baptisia Tinctoria 3X.

INDICATIONS:

May temporarily relieve dizziness and motion sickness with nausea.**

**Claims based on traditional homeopathic practice, not accepted medical evidence. Not FDA evaluated.

WARNINGS:

If pregnant or breast-feeding, ask a health professional before use.

Keep out of reach of children. In case of overdose, get medical help or contact a Poison Control Center right away.

Do not use if tamper evident seal is broken or missing. Store in a cool, dry place.

Keep out of reach of children. In case of overdose, get medical help or contact a Poison Control Center right away.

DIRECTIONS:

Adults and children 5 to 10 drops orally, 3 times daily or as otherwise directed by a health care professional. If symptoms persist for more than 7 days, consult your health care professional. Consult a physician for use in children under 12 years of age.

INDICATIONS:

May temporarily relieve dizziness and motion sickness with nausea.**

**Claims based on traditional homeopathic practice, not accepted medical evidence. Not FDA evaluated.

INACTIVE INGREDIENTS:

Demineralized water, 20% Ethanol

QUESTIONS:

Dist. by Energique, Inc.

201 Apple Blvd

Woodbine, IA 51579 800.869.8078

PACKAGE LABEL DISPLAY:

ENERGIQUE

SINCE 1987

HOMEOPATHIC REMEDY

VERTITONE

1 fl. oz. (30 ml)